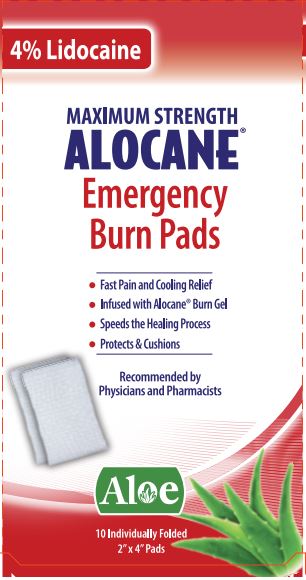 DRUG LABEL: Alocane Emergency Burn Pads
NDC: 68229-403 | Form: SWAB
Manufacturer: Quest Products, Inc.
Category: otc | Type: HUMAN OTC DRUG LABEL
Date: 20241105

ACTIVE INGREDIENTS: LIDOCAINE HYDROCHLORIDE 4 g/100 mL
INACTIVE INGREDIENTS: PROPANEDIOL; ALOE VERA LEAF; DIMETHYL ISOSORBIDE; HYDROXYETHYL CELLULOSE (5500 MPA.S AT 2%); PHENOXYETHANOL; CHLORPHENESIN; CAPRYLYL GLYCOL; .ALPHA.-TOCOPHEROL ACETATE; WATER

Alocane® Emergency Burn Pads

Drug Facts

Active Ingredient

Lidocaine HCL 4%

Purpose

Topical Analgesic

Uses

For the temporary relief of pain and itching associated with:

- Sunburn
- Minor Bums
- Minor Skin Irritation
- Cuts & Scrapes
- Insect Bites

Warnings

For external use only. Avoid contact with eyes.

Keep out of reach of children. In case of accidental ingestion, get medical help or contact a Poison Control Center right away.

Stop use and ask doctor: if condition worsens, or if symptoms persist for more than 7 days or clear up and occur again within a few days.

PREGNANCY OR BREAST FEEDING

If pregnant or breast-feeding, ask a health care professional before use.

Do not use in large quantities, particularly over raw surfaces or blistered areas.

Directions

Adults and children 2 years of age or older

- Clean the burn area with mild soap and water.
- Gently apply the Alocane• Pad over the burn or wound.
- Use on affected area not more than 3 to 4 times daily
- Children under 2 years of age consult a doctor.

Other Information

Store at room temperature 15-30ºC (59-86ºF)

Inactive Ingredients

1,3-Propanediol, Aloe Barbadensis (Aloe) leaf Juice, Caprylyl Glycol, Chlorphenesin, Dimethyl lsosorbide, Hydroxyethyl Cellulose, Phenoxyethanol, Tocopheryl Acetate (Vitamin E), Water.